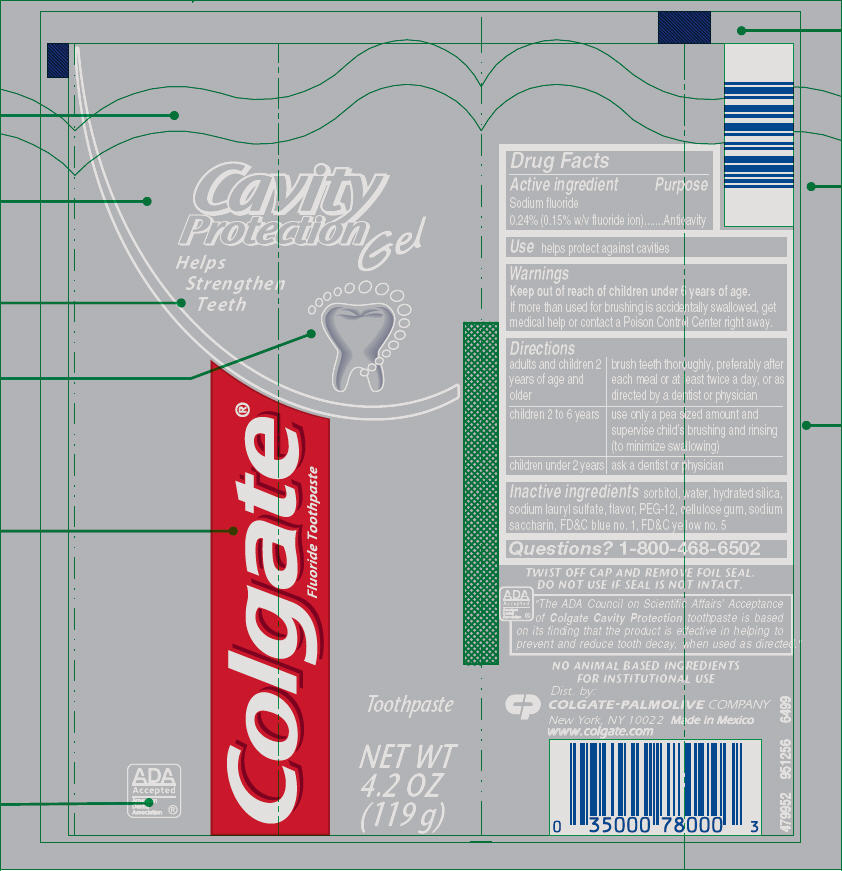 DRUG LABEL: Colgate  Cavity  Protection
NDC: 35000-953 | Form: GEL, DENTIFRICE
Manufacturer: Colgate-Palmolive Company
Category: otc | Type: HUMAN OTC DRUG LABEL
Date: 20191213

ACTIVE INGREDIENTS: SODIUM FLUORIDE 1.1 mg/1 g
INACTIVE INGREDIENTS: SORBITOL 680 mg/1 g; WATER; HYDRATED SILICA; SODIUM LAURYL SULFATE; POLYETHYLENE GLYCOL 600; CARBOXYMETHYLCELLULOSE SODIUM, UNSPECIFIED; SACCHARIN SODIUM; FD&C BLUE NO. 1; FD&C YELLOW NO. 5

Colgate® Cavity Protection Gel

Drug Facts

Active ingredient

Sodium fluoride 0.24% (0.15% w/v fluoride ion)

Purpose

Anticavity

Use

helps protect against cavities

Warnings

Keep out of reach of children under 6 years of age. If more than used for brushing is accidentally swallowed, get medical help or contact a Poison Control Center right away.

Directions

adults and children 2 years of age and older | brush teeth thoroughly, preferably after each meal or at least twice a day, or as directed by a dentist or physician
children 2 to 6 years | use only a pea sized amount and supervise child's brushing and rinsing (to minimize swallowing)
children under 2 years | ask a dentist or physician

Inactive ingredients

sorbitol, water, hydrated silica, sodium lauryl sulfate, flavor, PEG-12, cellulose gum, sodium saccharin, FD&C blue no. 1, FD&C yellow no. 5

Questions?

1-800-468-6502

Dist. by:
COLGATE-PALMOLIVE COMPANY
New York, NY 10022

PRINCIPAL DISPLAY PANEL - 119 g Tube Label

Cavity
Protection
Gel

Helps
Strengthen
Teeth

Colgate®
Fluoride Toothpaste

ADA
Accepted
American
Dental
Association

Toothpaste

NET WT
4.2 OZ
(119 g)